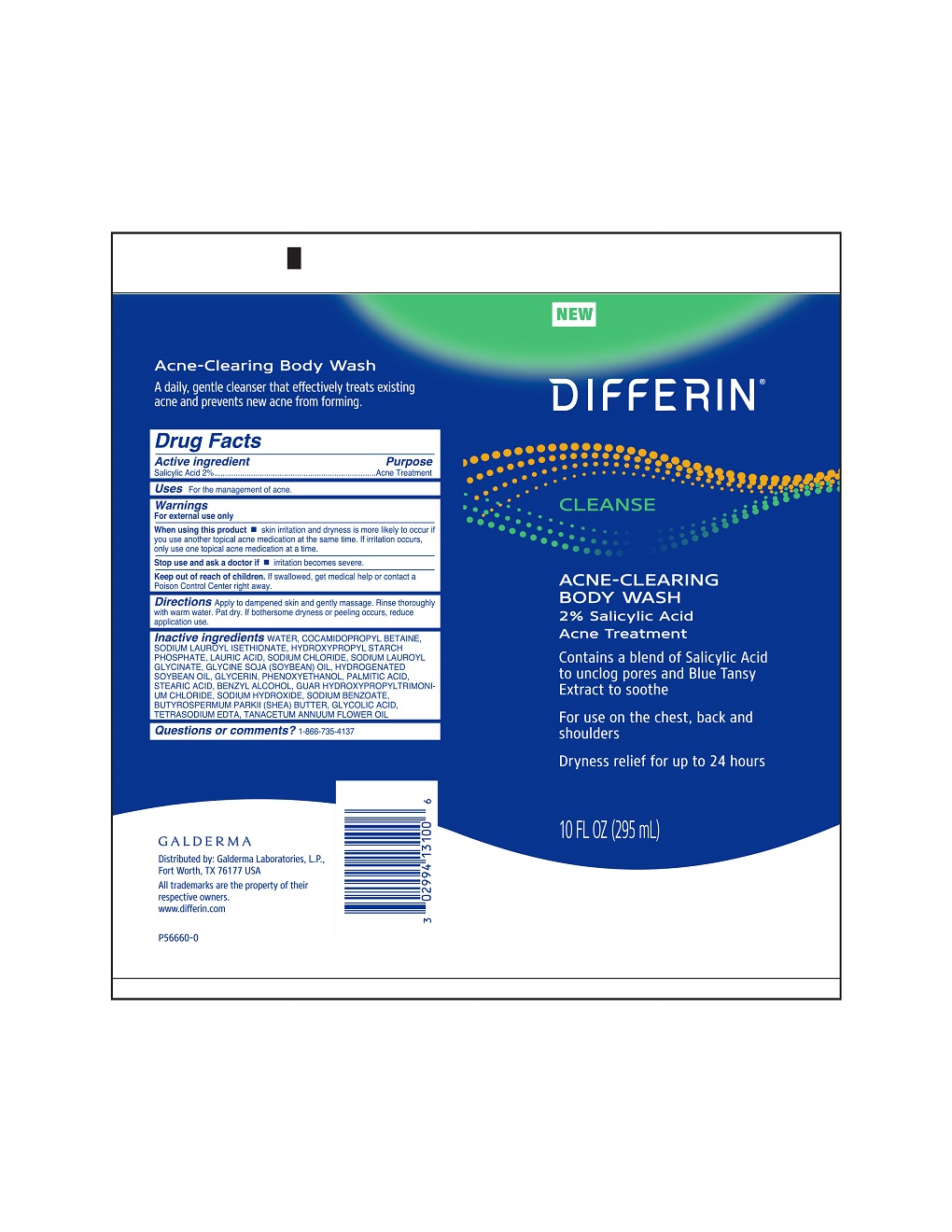 DRUG LABEL: Differin Acne Clearing Body Wash
NDC: 0299-4131 | Form: GEL
Manufacturer: Galderma Laboratories, L.P.
Category: otc | Type: HUMAN OTC DRUG LABEL
Date: 20231211

ACTIVE INGREDIENTS: Salicylic Acid 20 mg/1 mL
INACTIVE INGREDIENTS: Water; Cocamidopropyl Betaine; Sodium Lauroyl Isethionate; Lactic Acid, Unspecified Form; Sodium Chloride; Sodium Lauroyl Glycinate; Soybean Oil; Hydrogenated Soybean Oil; Glycerin; Phenoxyethanol; Palmitic Acid; Stearic Acid; Benzyl Alcohol; Guar Hydroxypropyltrimonium Chloride (1.7 Substituents Per Saccharide); Sodium Hydroxide; Sodium Benzoate; Shea Butter; Glycolic Acid; Edetate Sodium; Tanacetum Annuum Flowering Top Oil

Drug Facts

Active Ingredient

Salicylic Acid 2%

Purpose

Acne Treatment

Use

For the management of acne

Warnings

For external use only

When using this product

• skin irritation and dryness is more likely to occur if you use another topical acne medication at the same time. If irritation occurs, only use one topical acne medication at a time.

Stop use and ask a doctor if

• irritation becomes severe.

Keep out of reach of children.

If swallowed, get medical help or contact a Poison Control Center right away.

Directions

Apply to dampened skin and gently massage. Rinse thoroughly with warm water. Pat dry. If bothersome dryness of peeling occurs, reduce application use.

Inactive Ingredients

Water, Cocamidopropyl Betaine, Sodium Lauroyl Isethionate, Hydroxypropyl Starch Phosphate, Lauric Acid, Sodium Chloride, Sodium Lauroyl Glycinate, Glycine Soja (Soybean) Oil, Hydrogenated Soybean Oil, Glycerin, Phenoxyethanol, Palmitic Acid, Stearic Acid, Benzyl Alcohol, Guar Hydroxypropyltrimonium Chloride, Sodium Hydroxide, Sodium Benzoate, Butyrospermum Parkii (Shea) Butter, Glycolic Acid, Tetrasodium EDTA, Tanacetum Annuum Flower Oil

Questions or comments? 1-866-735-4137

Distributed by: Galderma Laboratories, L.P.,
Fort Worth, TX 76177 USA
All trademarks are the property of their respective owners.
www.differin.com
P56660-0

PRINCIPAL DISPLAY PANEL - 10 FL OZ tube

NEW
DIFFERIN®
CLEANSE

ACNE - CLEARING
BODY WASH

2% Salicylic Acid
Acne Treatment

Contains a blend of Salicylic Acid
to unclog pores and Blue Tansy
Extract to soothe

For use on the chest, back and
shoulders
Dryness relief for up to 24 hours

10 FL OZ (295 mL)